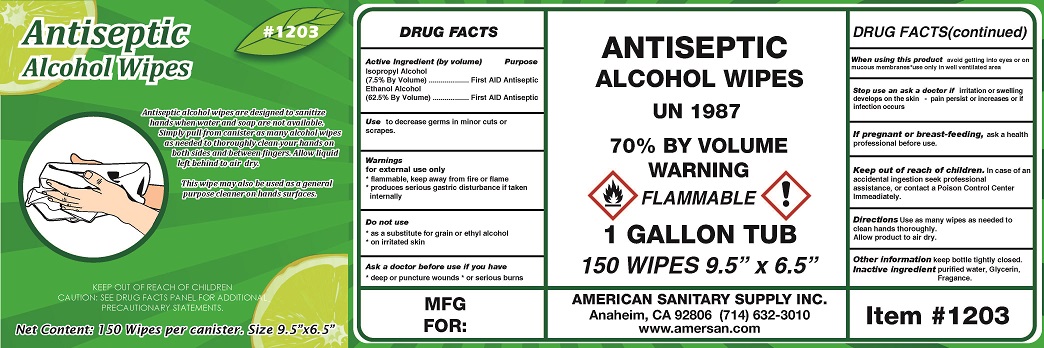 DRUG LABEL: ANTISEPTIC ALCOHOL WIPES
NDC: 50536-203 | Form: SOLUTION
Manufacturer: AMERICAN CHEMICAL AND SANITARY SUPPLY INC
Category: otc | Type: HUMAN OTC DRUG LABEL
Date: 20240509

ACTIVE INGREDIENTS: ALCOHOL 62.5 mL/1 1; ISOPROPYL ALCOHOL 7.5 mL/1 1
INACTIVE INGREDIENTS: WATER; GLYCERIN

AMERICAN CHEMICAL AND SANITARY SUPPLY - ANTISEPTIC ALCOHOL WIPES (50536-203)

ACTIVE INGREDIENT

ISOPROPYL ALCOHOL (7.5% BY VOLUME)

ETHANOL ALCOHOL (62.5% BY VOLUME)

PURPOSE

FIRST AID ANTISEPTIC

USE

TO DECREASE GERMS IN MINOR CUTS OR SCRAPES.

WARNINGS

FOR EXTERNAL USE ONLY

- FLAMMABLE, KEEP AWAY FROM FIRE OR FLAME
- PRODUCES SERIOUS GASTRIC DISTURBANCE IF TAKEN INTERNALLY

DO NOT USE

- AS A SUBSTITUTE FOR GRAIN OR ETHYL ALCOHOL
- ON IRRITATED SKIN

ASK A DOCTOR BEFORE USE IF YOU HAVE

- DEEP OR PUNCTURE WOUNDS
- OR SERIOUS BURNS

WHEN USING THIS PRODUCT AVOID GETTING INTO EYES OR ON MUCOUS MEMBRANES

- USE ONLY INA WELL VENTILATED AREA

STOP USE AND ASK A DOCTOR IF IRRITATION OR SWELLING DEVELOPS ON THE SKIN

- PAIN PERSIST OR INCREASES OR IF INFECTION OCURS

IF PREGNANT OR BREAST-FEEDING, ASK A HEALTH PROFESSIONAL BEFORE USE.

KEEP OUT OF REACH OF CHILDREN. IN CASE OF AN ACCIDENTAL INGESTION SEEK PROFESSIONAL ASSISTANCE, OR CONTACT A POISON CONTROL CENTER IMMEDIATELY.

DIRECTIONS

Use as many wipes as needed to clean hands thoroughly. Allow product to air dry.

OTHER INFORMATION

KEEP BOTTLE TIGHTLY CLOSED.

INACTIVE INGREDIENTS

purified water, Glycerin, Fragance.